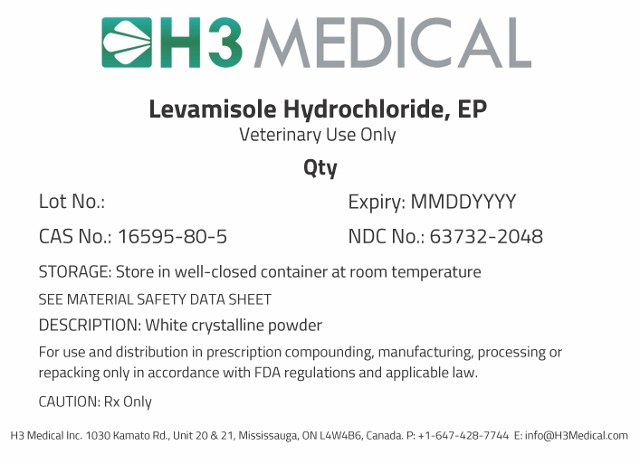 DRUG LABEL: Levamisole Hydrochloride
NDC: 63732-2048 | Form: POWDER
Manufacturer: H3 Medical Inc.
Category: other | Type: BULK INGREDIENT
Date: 20190904

ACTIVE INGREDIENTS: LEVAMISOLE HYDROCHLORIDE 1 g/1 g

Levamisole Hydrochloride